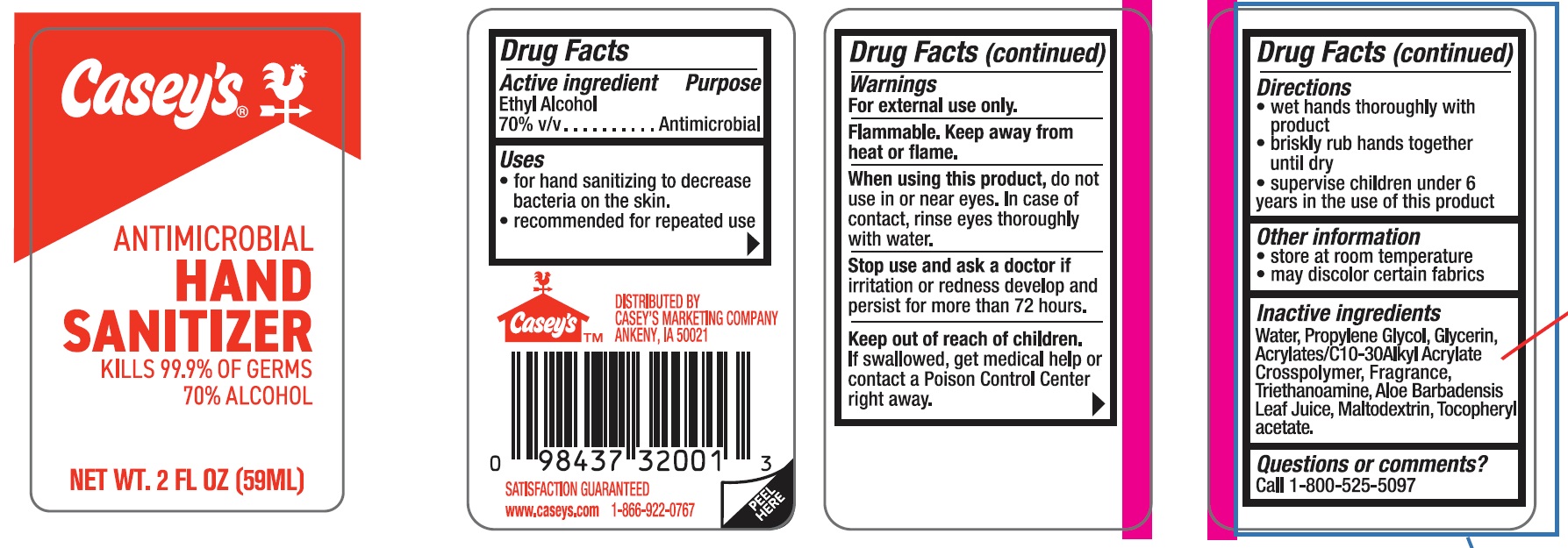 DRUG LABEL: Caseys Antimicrobial Hand Sanitizer
NDC: 67751-071 | Form: GEL
Manufacturer: Navajo Manufacturing Company Inc.
Category: otc | Type: HUMAN OTC DRUG LABEL
Date: 20240429

ACTIVE INGREDIENTS: ALCOHOL 70 mL/100 mL
INACTIVE INGREDIENTS: WATER; GLYCERIN; PROPYLENE GLYCOL; ACRYLATES/C10-30 ALKYL ACRYLATE CROSSPOLYMER (60000 MPA.S); TOCOPHERYL GLUCOSIDE; MALTODEXTRIN; ALOE ARBORESCENS LEAF; TRICLOSAN

67751-071

Active ingredient

Ethyl Alcohol, 70% v/v

Purpose Antimicrobial

Uses

- for hand sanitizing to decrease bacteria on the skin
- recommended for repeated use

Warnings

For external use only.

Flammable, keep away from heat or flame.

When using this product, do not use in or near the eyes. In case of contact, rinse eyes thoroughly with water

Stop use and ask a doctor if irritation or redness develop and persist for more than 72 hours

Keep out of reach of children. If swallowed, get medical help or contact a Poison Control Center right away.

Directions

- wet hands thoroughly with product
- briskly rub hands together until dry
- supervise children under 6 years in the use of this product

Other information

- store at room temperature
- may discolor certain fabrics

Inactive ingredients

Water (aqua), Propylene Glycol, Glycerin, Acrylates/C10-30 Alkyl Acrylate Crosspolymer, Fragrance, Triethanoamine, Aloe Barbadensis Leaf Juice, Maltodextrin, Tocopherylacetate